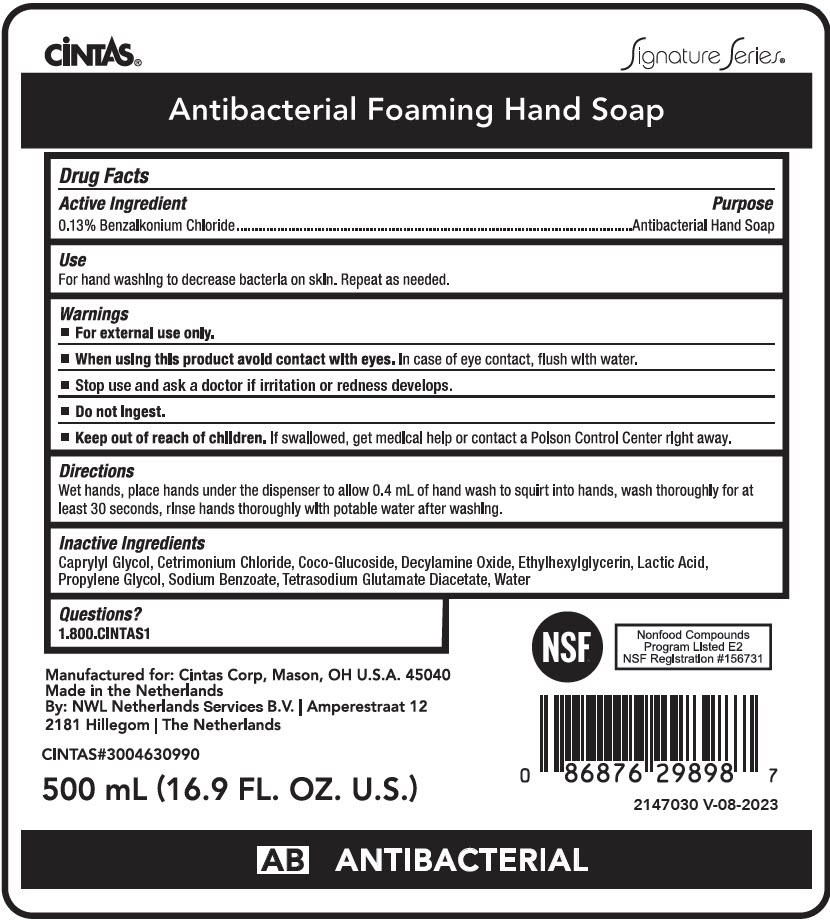 DRUG LABEL: Antibacterial Foaming Hand
NDC: 42961-615 | Form: SOAP
Manufacturer: Cintas
Category: otc | Type: HUMAN OTC DRUG LABEL
Date: 20260205

ACTIVE INGREDIENTS: BENZALKONIUM CHLORIDE 13 mg/10 mL
INACTIVE INGREDIENTS: WATER; CETRIMONIUM CHLORIDE; DECYLAMINE OXIDE; GLYCERIN; COCO-GLUCOSIDE; COCAMIDOPROPYLAMINE OXIDE; CITRIC ACID MONOHYDRATE; PHENOXYETHANOL; TETRASODIUM GLUTAMATE DIACETATE; SODIUM HYDROXIDE; SODIUM BENZOATE; LACTIC ACID, UNSPECIFIED FORM

Antibacterial Foaming Hand

Drug Facts

Active Ingredient

0.13% Benzalkonium Chloride

Purpose

Antibacterial Hand Soap

Use

For hand washing to decrease bacteria on skin. Repeat as neeeded.

Warnings

For external use only.

When using this product avoid contact with eyes. In case of eye contact, flush with water.

Stop use and ask a doctor, if irritation or redness persist.

Do not ingest.

Keep out of reach of children, if swallowed, get medical help or contact a Poison Control Center right away.

Directions

Wet hands, place hands under the dispenser to allow 0.4 mL of hand wash to squirt into hands, wash thoroughly for at least 30 seconds, rinse hands thoroughly with potable water after washing.

Inactive Ingredients

Caprylyl Glycol, Cetrimonium Chloride, Coco-Glucoside, Decylamine Oxide, Ethylhexylglycerin, Lactic Acid, Propylene Glycol, Sodium Benzoate, Tetrasodium Glutamate Diacetate, Water

Questions?

1.800.CINTAS1

PRINCIPAL DISPLAY PANEL - 500 mL Bag Label

CiNTAS®
Signature Series®

Antibacterial Foaming Hand Soap

CINTAS#3004630990

500 mL (16.9 FL. OZ. U.S.)

NSF®
Nonfood Compounds
Program Listed E2
NSF Registration #156731

2147030 V-08-2023

ANTIBACTERIAL